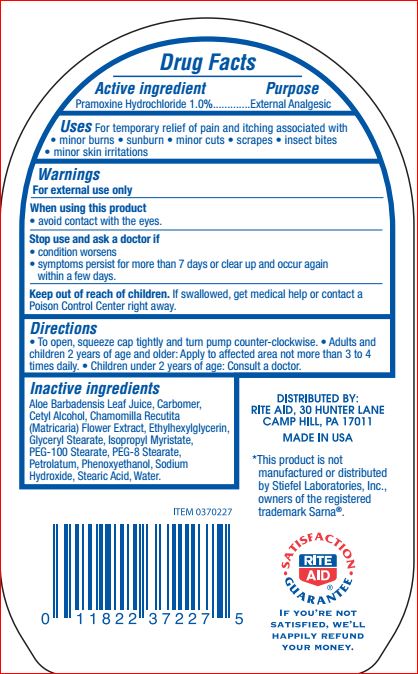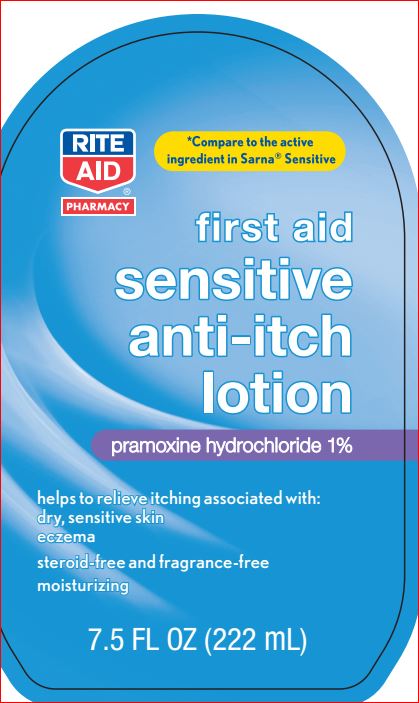 DRUG LABEL: First Aid Sensitive Anti-Itch
NDC: 11822-1236 | Form: LOTION
Manufacturer: Rite Aid
Category: otc | Type: HUMAN OTC DRUG LABEL
Date: 20180619

ACTIVE INGREDIENTS: Pramoxine Hydrochloride 1 g/100 mL
INACTIVE INGREDIENTS: ALOE VERA LEAF; CARBOMER HOMOPOLYMER TYPE C (ALLYL PENTAERYTHRITOL CROSSLINKED); Cetyl Alcohol; CHAMOMILE; Ethylhexylglycerin; GLYCERYL MONOSTEARATE; Isopropyl Myristate; PEG-100 Stearate; PEG-8 Stearate; Petrolatum; Phenoxyethanol; Sodium Hydroxide; Stearic Acid; Water

Drug Facts

Active ingredient Purpose
Pramoxine Hydrochloride 1.0%.............External Analgesic

Uses

For temporary relief of pain and itching associated with
• minor burns • sunburn • minor cuts • scrapes • insect bites
• minor skin irritations

Warnings
For external use only
When using this product
• avoid contact with the eyes.
Stop use and ask a doctor if
• condition worsens
• symptoms persist for more than 7 days or clear up and occur again
within a few days.

Keep out of reach of children. If swallowed, get medical help or contact a
Poison Control Center right away.

Directions
• To open, squeeze cap tightly and turn pump counter-clockwise. • Adults and
children 2 years of age and older: Apply to affected area not more than 3 to 4
times daily. • Children under 2 years of age: Consult a doctor

Inactive ingredients

Aloe Barbadensis Leaf Juice
Carbomer
Cetyl Alcohol
Chamomilla Recutita (Matricaria) Flower Extract
Ethylhexylglycerin
Glyceryl Stearate
Isopropyl Myristate
PEG-100 Stearate
PEG-8 Stearate
Petrolatum
Phenoxyethanol
Sodium Hydroxide
Stearic Acid
Water